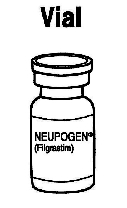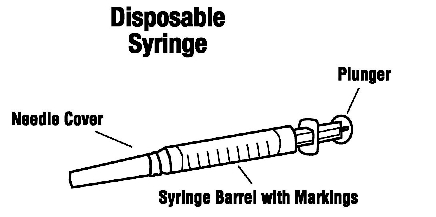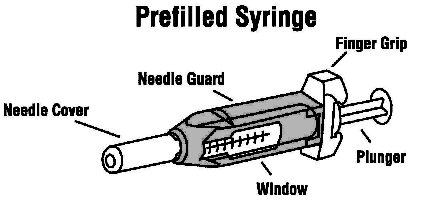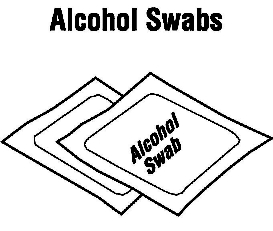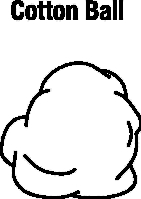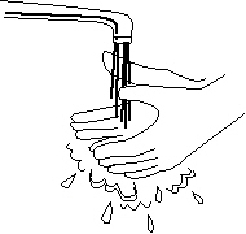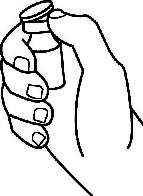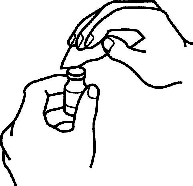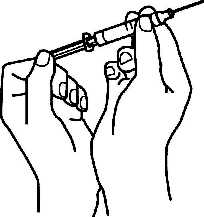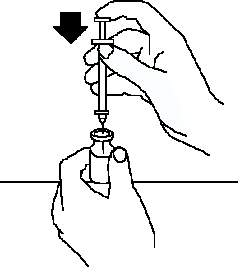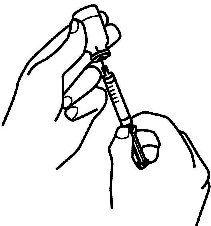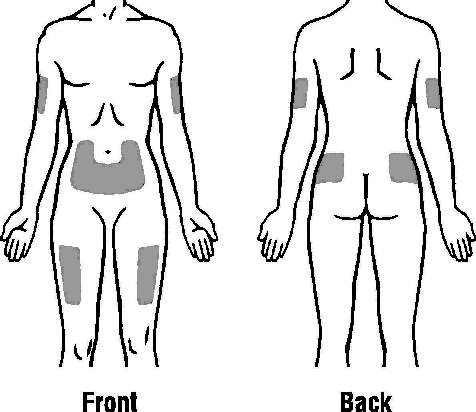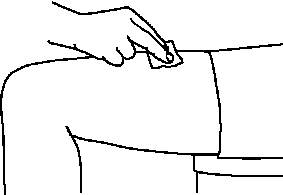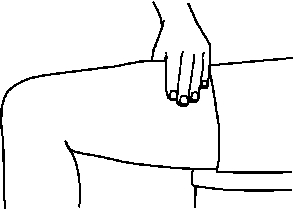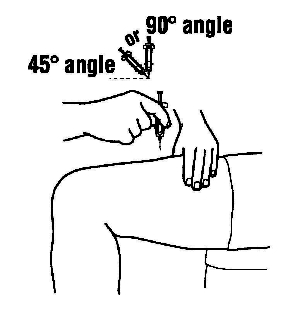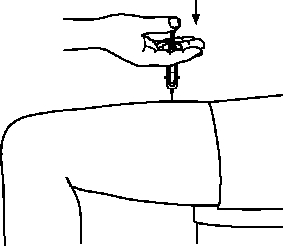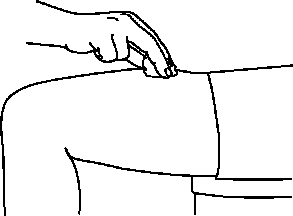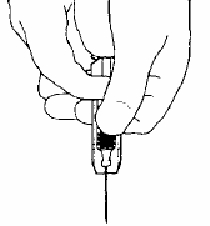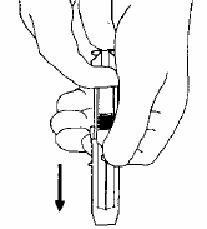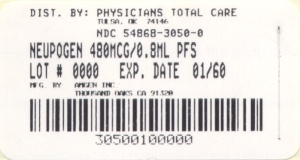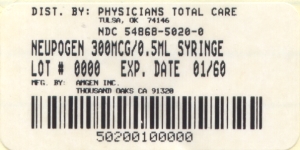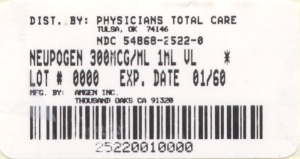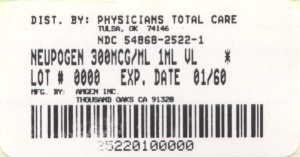 DRUG LABEL: Neupogen
NDC: 54868-2522 | Form: INJECTION, SOLUTION
Manufacturer: Physicians Total Care, Inc.
Category: prescription | Type: HUMAN PRESCRIPTION DRUG LABEL
Date: 20091202

ACTIVE INGREDIENTS: FILGRASTIM 300 ug/1 mL
INACTIVE INGREDIENTS: POLYSORBATE 80 0.04 mg/1.0 mL; SODIUM POLYMETAPHOSPHATE 0.035 mg/1.0 mL; SORBITOL 50.0 mg/1.0 mL; WATER

DESCRIPTION

Filgrastim is a human granulocyte colony-stimulating factor (G-CSF)‚ produced by recombinant DNA technology. NEUPOGEN® is the Amgen Inc. trademark for Filgrastim‚ which has been selected as the name for recombinant methionyl human granulocyte colony-stimulating factor (r-metHuG-CSF).

NEUPOGEN® is a 175 amino acid protein manufactured by recombinant DNA technology.^1 NEUPOGEN® is produced by Escherichia coli (E coli) bacteria into which has been inserted the human granulocyte colony-stimulating factor gene. NEUPOGEN® has a molecular weight of 18‚800 daltons. The protein has an amino acid sequence that is identical to the natural sequence predicted from human DNA sequence analysis‚ except for the addition of an N-terminal methionine necessary for expression in E coli. Because NEUPOGEN® is produced in E coli‚ the product is nonglycosylated and thus differs from G-CSF isolated from a human cell.

NEUPOGEN® is a sterile‚ clear‚ colorless‚ preservative-free liquid for parenteral administration containing Filgrastim at a specific activity of 1.0 ± 0.6 x 10^8 U/mg (as measured by a cell mitogenesis assay). The product is available in single use vials and prefilled syringes. The single use vials contain either 300 mcg or 480 mcg Filgrastim at a fill volume of 1.0 mL or 1.6 mL, respectively. The single use prefilled syringes contain either 300 mcg or 480 mcg Filgrastim at a fill volume of 0.5 mL or 0.8 mL, respectively. See table below for product composition of each single use vial or prefilled syringe.

 | 300 mcg/; 1.0 mL Vial | 480 mcg/; 1.6 mL Vial | 300 mcg/; 0.5 mL Syringe | 480 mcg/; 0.8 mL Syringe
Filgrastim | 300 mcg | 480 mcg | 300 mcg | 480 mcg
Acetate | 0.59 mg | 0.94 mg | 0.295 mg | 0.472 mg
Sorbitol | 50.0 mg | 80.0 mg | 25.0 mg | 40.0 mg
Polysorbate 80 | 0.04 mg | 0.064 mg | 0.02 mg | 0.032 mg
Sodium | 0.035 mg | 0.056 mg | 0.0175 mg | 0.028 mg
Water for Injection
USP q.s. ad | 1.0 mL | 1.6 mL | 0.5 mL | 0.8 mL

CLINICAL PHARMACOLOGY

Colony-stimulating Factors

Colony-stimulating factors are glycoproteins which act on hematopoietic cells by binding to specific cell surface receptors and stimulating proliferation‚ differentiation commitment‚ and some end-cell functional activation.

Endogenous G-CSF is a lineage specific colony-stimulating factor which is produced by monocytes‚ fibroblasts, and endothelial cells. G-CSF regulates the production of neutrophils within the bone marrow and affects neutrophil progenitor proliferation‚2‚3 differentiation,2‚4 and selected end-cell functional activation (including enhanced phagocytic ability‚^5 priming of the cellular metabolism associated with respiratory burst‚^6 antibody dependent killing,^7 and the increased expression of some functions associated with cell surface antigens^8). G-CSF is not species specific and has been shown to have minimal direct in vivo or in vitro effects on the production of hematopoietic cell types other than the neutrophil lineage.

Preclinical Experience

Filgrastim was administered to monkeys‚ dogs‚ hamsters‚ rats‚ and mice as part of a preclinical toxicology program which included single-dose acute‚ repeated-dose subacute‚ subchronic‚ and chronic studies. Single-dose administration of Filgrastim by the oral‚ intravenous (IV)‚ subcutaneous (SC)‚ or intraperitoneal (IP) routes resulted in no significant toxicity in mice‚ rats‚ hamsters‚ or monkeys. Although no deaths were observed in mice‚ rats‚ or monkeys at dose levels up to 3450 mcg/kg or in hamsters using single doses up to approximately 860 mcg/kg‚ deaths were observed in a subchronic (13-week) study in monkeys. In this study‚ evidence of neurological symptoms was seen in monkeys treated with doses of Filgrastim greater than 1150 mcg/kg/day for up to 18 days. Deaths were seen in 5 of the 8 treated animals and were associated with 15- to 28-fold increases in peripheral leukocyte counts‚ and neutrophil-infiltrated hemorrhagic foci were seen in both the cerebrum and cerebellum. In contrast‚ no monkeys died following 13 weeks of daily IV administration of Filgrastim at a dose level of 115 mcg/kg. In an ensuing 52-week study‚ one 115 mcg/kg dosed female monkey died after 18 weeks of daily IV administration of Filgrastim. Death was attributed to cardiopulmonary insufficiency.

In subacute‚ repeated-dose studies‚ changes observed were attributable to the expected pharmacological actions of Filgrastim (ie‚ dose-dependent increases in white cell counts‚ increased circulating segmented neutrophils‚ and increased myeloid:erythroid ratio in bone marrow). In all species‚ histopathologic examination of the liver and spleen revealed evidence of ongoing extramedullary granulopoiesis; increased spleen weights were seen in all species and appeared to be dose-related. A dose-dependent increase in serum alkaline phosphatase was observed in rats‚ and may reflect increased activity of osteoblasts and osteoclasts. Changes in serum chemistry values were reversible following discontinuation of treatment.

In rats treated at doses of 1150 mcg/kg/day for 4 weeks (5 of 32 animals) and for 13 weeks at doses of 100 mcg/kg/day (4 of 32 animals) and 500 mcg/kg/day (6 of 32 animals)‚ articular swelling of the hind legs was observed. Some degree of hind leg dysfunction was also observed; however‚ symptoms reversed following cessation of dosing. In rats‚ osteoclasis and osteoanagenesis were found in the femur‚ humerus‚ coccyx‚ and hind legs (where they were accompanied by synovitis) after IV treatment for 4 weeks (115 to 1150 mcg/kg/day)‚ and in the sternum after IV treatment for 13 weeks (115 to 575 mcg/kg/day). These effects reversed to normal within 4 to 5 weeks following cessation of treatment.

In the 52-week chronic‚ repeated-dose studies performed in rats (IP injection up to 57.5 mcg/kg/day)‚ and cynomolgus monkeys (IV injection of up to 115 mcg/kg/day)‚ changes observed were similar to those noted in the subacute studies. Expected pharmacological actions of Filgrastim included dose-dependent increases in white cell counts‚ increased circulating segmented neutrophils and alkaline phosphatase levels‚ and increased myeloid:erythroid ratios in the bone marrow. Decreases in platelet counts were also noted in primates. In no animals tested were hemorrhagic complications observed. Rats displayed dose-related swelling of the hind limb‚ accompanied by some degree of hind limb dysfunction; osteopathy was noted microscopically. Enlarged spleens (both species) and livers (monkeys)‚ reflective of ongoing extramedullary granulopoiesis‚ as well as myeloid hyperplasia of the bone marrow‚ were observed in a dose-dependent manner.

Pharmacologic Effects of NEUPOGEN®

In phase 1 studies involving 96 patients with various nonmyeloid malignancies‚ NEUPOGEN® administration resulted in a dose-dependent increase in circulating neutrophil counts over the dose range of 1 to 70 mcg/kg/day.^9-11 This increase in neutrophil counts was observed whether NEUPOGEN® was administered IV (1 to 70 mcg/kg twice daily)‚^9 SC (1 to 3 mcg/kg once daily)‚^11 or by continuous SC infusion (3 to 11 mcg/kg/day).^10 With discontinuation of NEUPOGEN® therapy‚ neutrophil counts returned to baseline‚ in most cases within 4 days. Isolated neutrophils displayed normal phagocytic (measured by zymosan-stimulated chemoluminescence) and chemotactic (measured by migration under agarose using N-formyl-methionyl-leucyl-phenylalanine [fMLP] as the chemotaxin) activity in vitro.

The absolute monocyte count was reported to increase in a dose-dependent manner in most patients receiving NEUPOGEN®; however‚ the percentage of monocytes in the differential count remained within the normal range. In all studies to date‚ absolute counts of both eosinophils and basophils did not change and were within the normal range following administration of NEUPOGEN®. Increases in lymphocyte counts following NEUPOGEN® administration have been reported in some normal subjects and cancer patients.

White blood cell (WBC) differentials obtained during clinical trials have demonstrated a shift towards earlier granulocyte progenitor cells (left shift)‚ including the appearance of promyelocytes and myeloblasts‚ usually during neutrophil recovery following the chemotherapy-induced nadir. In addition‚ Dohle bodies‚ increased granulocyte granulation‚ and hypersegmented neutrophils have been observed. Such changes were transient and were not associated with clinical sequelae, nor were they necessarily associated with infection.

Pharmacokinetics

Absorption and clearance of NEUPOGEN® follows first-order pharmacokinetic modeling without apparent concentration dependence. A positive linear correlation occurred between the parenteral dose and both the serum concentration and area under the concentration-time curves. Continuous IV infusion of 20 mcg/kg of NEUPOGEN® over 24 hours resulted in mean and median serum concentrations of approximately 48 and 56 ng/mL‚ respectively. Subcutaneous administration of 3.45 mcg/kg and 11.5 mcg/kg resulted in maximum serum concentrations of 4 and 49 ng/mL‚ respectively‚ within 2 to 8 hours. The volume of distribution averaged 150 mL/kg in both normal subjects and cancer patients. The elimination half-life‚ in both normal subjects and cancer patients‚ was approximately 3.5 hours. Clearance rates of NEUPOGEN® were approximately 0.5 to 0.7 mL/minute/kg. Single parenteral doses or daily IV doses‚ over a 14-day period‚ resulted in comparable half-lives. The half-lives were similar for IV administration (231 minutes‚ following doses of 34.5 mcg/kg) and for SC administration (210 minutes‚ following NEUPOGEN® doses of 3.45 mcg/kg). Continuous 24-hour IV infusions of 20 mcg/kg over an 11- to 20-day period produced steady-state serum concentrations of NEUPOGEN® with no evidence of drug accumulation over the time period investigated.

Pharmacokinetic data in geriatric patients (≥ 65 years) are not available.

CLINICAL EXPERIENCE

Cancer Patients Receiving Myelosuppressive Chemotherapy

NEUPOGEN® has been shown to be safe and effective in accelerating the recovery of neutrophil counts following a variety of chemotherapy regimens. In a phase 3 clinical trial in small cell lung cancer‚ patients received SC administration of NEUPOGEN® (4 to 8 mcg/kg/day‚ days 4 to 17) or placebo. In this study‚ the benefits of NEUPOGEN® therapy were shown to be prevention of infection as manifested by febrile neutropenia‚ decreased hospitalization‚ and decreased IV antibiotic usage. No difference in survival or disease progression was demonstrated.

In the phase 3‚ randomized‚ double-blind‚ placebo-controlled trial conducted in patients with small cell lung cancer‚ patients were randomized to receive NEUPOGEN® (n = 99) or placebo (n = 111) starting on day 4‚ after receiving standard dose chemotherapy with cyclophosphamide‚ doxorubicin‚ and etoposide. A total of 210 patients were evaluated for efficacy and 207 evaluated for safety. Treatment with NEUPOGEN® resulted in a clinically and statistically significant reduction in the incidence of infection‚ as manifested by febrile neutropenia; the incidence of at least one infection over all cycles of chemotherapy was 76% (84/111) for placebo-treated patients‚ versus 40% (40/99) for NEUPOGEN®-treated patients (p less than 0.001). The following secondary analyses were also performed. The requirements for in-patient hospitalization and antibiotic use were also significantly decreased during the first cycle of chemotherapy; incidence of hospitalization was 69% (77/111) for placebo-treated patients in cycle 1‚ versus 52% (51/99) for NEUPOGEN®-treated patients (p = 0.032). The incidence of IV antibiotic usage was 60% (67/111) for placebo-treated patients in cycle 1‚ versus 38% (38/99) for NEUPOGEN®-treated patients (p = 0.003). The incidence‚ severity‚ and duration of severe neutropenia (absolute neutrophil count [ANC] less than 500/mm^3) following chemotherapy were all significantly reduced. The incidence of severe neutropenia in cycle 1 was 84% (83/99) for patients receiving NEUPOGEN® versus 96% (106/110) for patients receiving placebo (p = 0.004). Over all cycles‚ patients randomized to NEUPOGEN® had a 57% (286/500 cycles) rate of severe neutropenia versus 77% (416/543 cycles) for patients randomized to placebo. The median duration of severe neutropenia in cycle 1 was reduced from 6 days (range 0 to 10 days) for patients receiving placebo to 2 days (range 0 to 9 days) for patients receiving NEUPOGEN® (p less than 0.001). The mean duration of neutropenia in cycle 1 was 5.64 ± 2.27 days for patients receiving placebo versus 2.44 ± 1.90 days for patients receiving NEUPOGEN®. Over all cycles‚ the median duration of neutropenia was 3 days for patients randomized to placebo versus 1 day for patients randomized to NEUPOGEN®. The median severity of neutropenia (as measured by ANC nadir) was 72/mm^3 (range 0/mm^3 to 7912/mm^3) in cycle 1 for patients receiving NEUPOGEN® versus 38/mm^3 (range 0/mm^3 to 9520/mm^3) for patients receiving placebo (p = 0.012). The mean severity of neutropenia in cycle 1 was 496/mm^3 ± 1382/mm^3 for patients receiving NEUPOGEN® versus 204/mm^3 ± 953/mm^3 for patients receiving placebo. Over all cycles‚ the ANC nadir for patients randomized to NEUPOGEN® was 403/mm3‚ versus 161/mm^3 for patients randomized to placebo. Administration of NEUPOGEN® resulted in an earlier ANC nadir following chemotherapy than was experienced by patients receiving placebo (day 10 vs day 12). NEUPOGEN® was well tolerated when given SC daily at doses of 4 to 8 mcg/kg for up to 14 consecutive days following each cycle of chemotherapy (see ADVERSE REACTIONS).

Several other phase 1/2 studies‚ which did not directly measure the incidence of infection‚ but which did measure increases in neutrophils‚ support the efficacy of NEUPOGEN®. The regimens are presented to provide some background on the clinical experience with NEUPOGEN®. No claim regarding the safety or efficacy of the chemotherapy regimens is made. The effects of NEUPOGEN® on tumor growth or on the anti-tumor activity of the chemotherapy were not assessed. The doses of NEUPOGEN® used in these studies are considerably greater than those found to be effective in the phase 3 study described above. Such phase 1/2 studies are summarized in the following table.

Type of Malignacy | Regimen | Chemotherapy Dose | No. Pts. | Trial Phase | NEUPOGEN® Daily Dosage*
Small Cell
Lung Cancer | Cyclophosphamide | 1 g/m^2/day | 210 | 3 | 4 - 8 mcg/kg SC
 | Doxorubicin | 50 mg/m^2/day |  |  | days 4 - 17
 | Etoposide | 120 mg/m^2/day x 3
 |  | q 21 days
Small Cell
Lung Cancer^11 | Ifosfamide | 5 g/m^2/day | 12 | 1/2 | 5.75 - 46 mcg/kg IV
 | Doxorubicin | 50 mg/m^2/day |  |  | days 4 - 17
 | Etoposide | 120 mg/m^2/day x 3
 | Mesna | 8 g/m^2/day
 |  | q 21 days
Urothelial |  | |
Cancer^12 | Methotrexate | 30 mg/m^2/day x 2 | 40 | 1/2 | 3.45 - 69 mcg/kg IV
 | Vinblastine | 3 mg/m^2/day x 2 |  |  | days 4 - 11
 | Doxorubicin | 30 mg/m^2/day
 | Cisplatin | 70 mg/m^2/day
 |  | q 28 days
Various |  | |
Nonmyeloid |  | |
Malignancies^13 | Cyclophosphamide | 2.5 g/m^2/day x 2 | 18 | 1/2 | 23 - 69 mcg/kg† IV
 | Etoposide | 500 mg/m^2/day x 3 |  |  | days 8 - 28
 | Cisplatin | 50 mg/m^2/day x 3
 |  | q 28 days
Breast/Ovarian |  | |
Cancer^14 | Doxorubicin‡ | 75 mg/m^2 | 21 | 2 | 11.5 mcg/kg IV
 |  | 100 mg/m^2 |  |  | days 2 - 9
 |  | 125 mg/m^2 |  |  | 5.75 mcg/kg IV
 |  | 150 mg/m^2 |  |  | days 10 - 12
 |  | q 14 days
Neuroblastoma | Cyclophosphamide | 150 mg/m^2 x 7 | 12 | 2 | 5.45 - 17.25 mcg/kg SC
 | Doxorubicin | 35 mg/m^2 |  |  | days 6 - 19
75 mg/m^2 | Cisplatin | 90 mg/m^2
 |  | q 28 days
 |  | (cycles 1‚3‚5)§

* NEU® doses were those that accelerated neutrophil production. Doses which provided no additional acceleration beyond that achieved at the next lower dose are not reported.
† Lowest dose(s) tested in the study.
‡ Patients received doxorubicin at either 75‚ 100‚ 125‚ or 150 mg/m^2.
§ Cycles 2‚6 = cyclophosphamide 150 mg/m^2 x 7 and etoposide 280 mg/m^2 x 3.
Cycle 4 = cisplatin 90 mg/m^2 x 1 and etoposide 280 mg/m^2 x 3.
Patients With Acute Myeloid Leukemia Receiving Induction or Consolidation Chemotherapy

In a randomized, double-blind‚ placebo-controlled‚ multi-center‚ phase 3 clinical trial‚ 521 patients (median age 54‚ range 16 to 89 years) were treated for de novo acute myeloid leukemia (AML). Following a standard induction chemotherapy regimen comprising daunorubicin, cytosine arabinoside, and etoposide^15 (DAV 3+7+5), patients received either NEUPOGEN® at 5 mcg/kg/day or placebo, SC, from 24 hours after the last dose of chemotherapy until neutrophil recovery (ANC 1000/mm^3 for 3 consecutive days or 10,000/mm^3 for 1 day) or for a maximum of 35 days.

Treatment with NEUPOGEN® significantly reduced the median time to ANC recovery and the median duration of fever, antibiotic use, and hospitalization following induction chemotherapy. In the NEUPOGEN®-treated group‚ the median time from initiation of chemotherapy to ANC recovery (ANC greater than or equal to 500/mm^3) was 20 days (vs 25 days in the control group, p = 0.0001), the median duration of fever was reduced by 1.5 days (p = 0.009), and there were statistically significant reductions in the durations of IV antibiotic use and hospitalization. During consolidation therapy (DAV 2+5+5), patients treated with NEUPOGEN® also experienced significant reductions in the incidence of severe neutropenia, time to neutrophil recovery, the incidence and duration of fever, and the durations of IV antibiotic use and hospitalization. Patients treated with a further course of standard (DAV 2+5+5) or high-dose cytosine arabinoside consolidation also experienced significant reductions in the duration of neutropenia.

There were no statistically significant differences between NEUPOGEN® and placebo groups in complete remission rate (69% NEUPOGEN® vs 68% placebo, p = 0.77), disease-free survival (median 342 days NEUPOGEN® [n = 178], 322 days placebo [n = 177], p = 0.99), time to progression of all randomized patients (median 165 days NEUPOGEN®, 186 days placebo, p = 0.87), or overall survival (median 380 days NEUPOGEN®, 425 days placebo, p = 0.83).

Cancer Patients Receiving Bone Marrow Transplant

In two separate randomized‚ controlled trials‚ patients with Hodgkin’s disease (HD) and non-Hodgkin’s lymphoma (NHL) were treated with myeloablative chemotherapy and autologous bone marrow transplantation (ABMT). In one study (n = 54)‚ NEUPOGEN® was administered at doses of 10 or 30 mcg/kg/day; a third treatment group in this study received no NEUPOGEN®. A statistically significant reduction in the median number of days of severe neutropenia (ANC less than 500/mm^3) occurred in the NEUPOGEN®-treated group versus the control group (23 days in the control group‚ 11 days in the 10 mcg/kg/day group‚ and 14 days in the 30 mcg/kg/day group [11 days in the combined treatment groups‚ p = 0.004]). In the second study (n = 44‚ 43 patients evaluable)‚ NEUPOGEN® was administered at doses of 10 or 20 mcg/kg/day; a third treatment group in this study received no NEUPOGEN®. A statistically significant reduction in the median number of days of severe neutropenia occurred in the NEUPOGEN®-treated group versus the control group (21.5 days in the control group and 10 days in both treatment groups‚ p less than 0.001). The number of days of febrile neutropenia was also reduced significantly in this study (13.5 days in the control group‚ 5 days in the 10 mcg/kg/day group‚ and 5.5 days in the 20 mcg/kg/day group [5 days in the combined treatment groups‚ p less than 0.0001]). Reductions in the number of days of hospitalization and antibiotic use were also seen‚ although these reductions were not statistically significant. There were no effects on red blood cell or platelet levels.

In a randomized‚ placebo-controlled trial‚ 70 patients with myeloid and nonmyeloid malignancies were treated with myeloablative therapy and allogeneic bone marrow transplant followed by 300 mcg/m^2/day of a Filgrastim product. A statistically significant reduction in the median number of days of severe neutropenia occurred in the treated group versus the control group (19 days in the control group and 15 days in the treatment group‚ p less than 0.001) and time to recovery of ANC to greater than or equal to 500/mm^3 (21 days in the control group and 16 days in the treatment group‚ p less than 0.001).

In three nonrandomized studies (n = 119)‚ patients received ABMT and treatment with NEUPOGEN®. One study (n = 45) involved patients with breast cancer and malignant melanoma. A second study (n = 39) involved patients with HD. The third study (n = 35) involved patients with NHL‚ acute lymphoblastic leukemia (ALL)‚ and germ cell tumor. In these studies‚ the recovery of the ANC to greater than or equal to 500/mm^3 ranged from a median of 11.5 to 13 days.

None of the conditioning regimens used in the ABMT studies included radiation therapy.

While these studies were not designed to compare survival‚ this information was collected and evaluated. The overall survival and disease progression of patients receiving NEUPOGEN® in these studies were similar to those observed in the respective control groups and to historical data.

Peripheral Blood Progenitor Cell Collection and Therapy in Cancer Patients

All patients in the Amgen-sponsored trials received a similar mobilization/collection regimen: NEUPOGEN® was administered for 6 to 7 days‚ with an apheresis procedure on days 5‚ 6, and 7 (except for a limited number of patients receiving apheresis on days 4‚ 6, and 8). In a non-Amgen-sponsored study‚ patients underwent mobilization to a target number of mononuclear cells (MNC)‚ with apheresis starting on day 5. There are no data on the mobilization of peripheral blood progenitor cells (PBPC) after days 4 to 5 that are not confounded by leukapheresis.

Mobilization: Mobilization of PBPC was studied in 50 heavily pretreated patients (median number of prior cycles = 9.5) with NHL‚ HD, or ALL (Amgen study 1). CFU-GM was used as the marker for engraftable PBPC. The median CFU-GM level on each day of mobilization was determined from the data available (CFU-GM assays were not obtained on all patients on each day of mobilization). These data are presented below.

The data from Amgen study 1 were supported by data from Amgen study 2 in which 22 pretreated breast cancer patients (median number of prior cycles = 3) were studied. Both the CFU-GM and CD34^+ cells reached a maximum on day 5 at greater than 10-fold over baseline and then remained elevated with leukapheresis.

Progenitor Cell Levels in Peripheral Blood by Mobilization Day
 | No. Samples | Median (25% - 75%) | No. Samples | Median (25% - 75%) | No. Samples | Median (25% - 75%)
Day 1 | 11 | 18 (13 - 62) | 20 | 42 (15 - 151) | 20 | 0.13 (0.02 - 0.66)
Day 2 | 7 | 22 (3 - 61) | n/a* | n/a* | n/a* | n/a*
Day 3 | 10 | 138 (39 - 364) | n/a* | n/a* | n/a* | n/a*
Day 4 | 18 | 365 (158 - 864) | 18 | 576 (108 - 1819) | 17 | 2.11 (0.58 - 3.93)
Day 5 | 36 | 781 (391 - 1608) | 21 | 960 (72 - 1677) | 22 | 3.16 (1.08 - 6.11)
Day 6 | 46 | 505 (199 - 1397) | 22 | 756 (70 - 3486) | 22 | 2.67 (1.09 - 4.40)
Day 7 | 37 | 333 (111 - 938) | 22 | 597 (118 - 2009) | 21 | 2.64 (0.78 - 4.22)
Day 8 | 15 | 383 (94 - 815) | 12 | 51 (10 -746) | 12 | 1.61 (0.38 - 4.31)

* n/a = not available

In three studies of patients with prior exposure to chemotherapy‚ the median CFU-GM yield in the leukapheresis product ranged from 20.9 to 32.7 x 10^4/kg body weight (n = 105). In two of these studies where CD34^+ yields in the leukapheresis product were also determined‚ the median CD34^+ yields were 3.11 and 2.80 x 10^6/kg, respectively (n = 56). In an additional study of 18 chemotherapy-naive patients‚ the median CFU-GM yield was 123.4 x 10^4/kg.

Engraftment: Engraftment following NEUPOGEN®-mobilized PBPC is summarized for 101 patients in the following table. In all studies, a Cox regression model showed that the total number of CFU-GM and/or CD34^+ cells collected was a significant predictor of time to platelet recovery.

In a randomized, unblinded study of patients with HD or NHL undergoing myeloablative chemotherapy (Amgen study 3)‚ 27 patients received NEUPOGEN®-mobilized PBPC followed by NEUPOGEN® and 31 patients received ABMT followed by NEUPOGEN®. Patients randomized to the NEUPOGEN®-mobilized PBPC group compared to the ABMT group had significantly fewer days of platelet transfusions (median 6 vs 10 days)‚ a significantly shorter time to a sustained platelet count greater than 20‚000/mm^3 (median 16 vs 23 days)‚ a significantly shorter time to recovery of a sustained ANC greater than or equal to 500/mm^3 (median 11 vs 14 days)‚ significantly fewer days of red blood cell transfusions (median 2 vs 3 days) and a significantly shorter duration of posttransplant hospitalization.

 |  | Amgen-sponsored Study 1 N = 13 | Amgen-sponsored Study 2 N = 22 | Amgen-sponsored Study 3 N = 27 | Non-Amgen- sponsored Study N = 39
Median PBPC/kg Collected | MNC | 9.5 x 10^8 | 9.5 x 10^8 | 8.1 x 10^8 | 10.3 x 10^8
 | CD34^+ | n/a* | 3.1 x 10^6 | 2.8 x 10^6 | 6.2 x 10^6
 | CFU-GM | 63.9 x 10^4 | 25.3 x 10^4 | 32.6 x 10^4 | n/a*
Days to ANC ≥ 500/mm^3 | Median | 9 | 10 | 11 | 10
 | Range | 8 - 10 | 8 - 15 | 9 - 38 | 7 - 40
Days to Plt. ≥ 20,00/mm^3 | Median | 10 | 12.5 | 16 | 15.5
 | Range | 7 - 16 | 10 - 30 | 8 - 52 | 7 - 63

* n/a = not available

Three of the 101 patients (3%) did not achieve the criteria for engraftment as defined by a platelet count greater than or equal to 20‚000/mm^3 by day 28. In clinical trials of NEUPOGEN® for the mobilization of PBPC‚ NEUPOGEN® was administered to patients at 5 to 24 mcg/kg/day after reinfusion of the collected cells until a sustainable ANC (greater than or equal to 500/mm^3) was reached. The rate of engraftment of these cells in the absence of NEUPOGEN® posttransplantation has not been studied.

Patients With Severe Chronic Neutropenia

Severe chronic neutropenia (SCN) (idiopathic‚ cyclic‚ and congenital) is characterized by a selective decrease in the number of circulating neutrophils and an enhanced susceptibility to bacterial infections.

The daily administration of NEUPOGEN® has been shown to be safe and effective in causing a sustained increase in the neutrophil count and a decrease in infectious morbidity in children and adults with the clinical syndrome of SCN.^16 In the phase 3 trial‚ summarized in the following table‚ daily treatment with NEUPOGEN® resulted in significant beneficial changes in the incidence and duration of infection‚ fever‚ antibiotic use‚ and oropharyngeal ulcers. In this trial‚ 120 patients with a median age of 12 years (range 1 to 76 years) were treated.

Overall Significant Changes in Clinical Endpoints Median Incidence* (events) or Duration (days) per 28-day Period
 | Control Patients† | NEUPOGEN® -treated Patients | p-value
Incidence of Infection | 0.50 | 0.20 | less than 0.001
Incidence of Fever | 0.25 | 0.20 | less than 0.001
Duration of Fever | 0.63 | 0.20 | 0.005
Incidence of Oropharyngeal Ulcers | 0.26 | 0.00 | less than 0.001
Incidence of Antibiotic Use | 0.49 | 0.20 | less than 0.001

* Incidence values were calculated for each patient‚ and are defined as the total number of events experienced divided by the number of 28-day periods of exposure (on-study). Median incidence values were then reported for each patient group.
† Control patients were observed for a 4-month period.

The incidence for each of these 5 clinical parameters was lower in the NEUPOGEN® arm compared to the control arm for cohorts in each of the 3 major diagnostic categories. All 3 diagnostic groups showed favorable trends in favor of treatment. An analysis of variance showed no significant interaction between treatment and diagnosis‚ suggesting that efficacy did not differ substantially in the different diseases. Although NEUPOGEN® substantially reduced neutropenia in all patient groups‚ in patients with cyclic neutropenia‚ cycling persisted but the period of neutropenia was shortened to 1 day.

As a result of the lower incidence and duration of infections‚ there was also a lower number of episodes of hospitalization (28 hospitalizations in 62 patients in the treated group vs 44 hospitalizations in 60 patients in the control group over a 4-month period [p = 0.0034]). Patients treated with NEUPOGEN® also reported a lower number of episodes of diarrhea‚ nausea‚ fatigue‚ and sore throat.

In the phase 3 trial‚ untreated patients had a median ANC of 210/mm^3 (range 0 to 1550/mm^3). NEUPOGEN® therapy was adjusted to maintain the median ANC between 1500 and 10‚000/mm^3. Overall‚ the response to NEUPOGEN® was observed in 1 to 2 weeks. The median ANC after 5 months of NEUPOGEN® therapy for all patients was 7460/mm^3 (range 30 to 30‚880/mm^3). NEUPOGEN® dosing requirements were generally higher for patients with congenital neutropenia (2.3 to 40 mcg/kg/day) than for patients with idiopathic (0.6 to 11.5 mcg/kg/day) or cyclic (0.5 to 6 mcg/kg/day) neutropenia.

INDICATIONS AND USAGE

Cancer Patients Receiving Myelosuppressive Chemotherapy

NEUPOGEN® is indicated to decrease the incidence of infection‚ as manifested by febrile neutropenia‚ in patients with nonmyeloid malignancies receiving myelosuppressive anti-cancer drugs associated with a significant incidence of severe neutropenia with fever (see CLINICAL EXPERIENCE). A complete blood count (CBC) and platelet count should be obtained prior to chemotherapy‚ and twice per week (see LABORATORY MONITORING) during NEUPOGEN® therapy to avoid leukocytosis and to monitor the neutrophil count. In phase 3 clinical studies‚ NEUPOGEN® therapy was discontinued when the ANC was ≥ 10‚000/mm^3 after the expected chemotherapy-induced nadir.

Patients With Acute Myeloid Leukemia Receiving Induction or Consolidation Chemotherapy

NEUPOGEN® is indicated for reducing the time to neutrophil recovery and the duration of fever, following induction or consolidation chemotherapy treatment of adults with AML.

Cancer Patients Receiving Bone Marrow Transplant

NEUPOGEN® is indicated to reduce the duration of neutropenia and neutropenia-related clinical sequelae‚ eg‚ febrile neutropenia‚ in patients with nonmyeloid malignancies undergoing myeloablative chemotherapy followed by marrow transplantation (see CLINICAL EXPERIENCE). It is recommended that CBCs and platelet counts be obtained at a minimum of 3 times per week (see LABORATORY MONITORING) following marrow infusion to monitor the recovery of marrow reconstitution.

Patients Undergoing Peripheral Blood Progenitor Cell Collection and Therapy

NEUPOGEN® is indicated for the mobilization of hematopoietic progenitor cells into the peripheral blood for collection by leukapheresis. Mobilization allows for the collection of increased numbers of progenitor cells capable of engraftment compared with collection by leukapheresis without mobilization or bone marrow harvest. After myeloablative chemotherapy‚ the transplantation of an increased number of progenitor cells can lead to more rapid engraftment‚ which may result in a decreased need for supportive care (see CLINICAL EXPERIENCE).

Patients With Severe Chronic Neutropenia

NEUPOGEN® is indicated for chronic administration to reduce the incidence and duration of sequelae of neutropenia (eg‚ fever‚ infections‚ oropharyngeal ulcers) in symptomatic patients with congenital neutropenia‚ cyclic neutropenia‚ or idiopathic neutropenia (see CLINICAL EXPERIENCE). It is essential that serial CBCs with differential and platelet counts‚ and an evaluation of bone marrow morphology and karyotype be performed prior to initiation of NEUPOGEN® therapy (see WARNINGS). The use of NEUPOGEN® prior to confirmation of SCN may impair diagnostic efforts and may thus impair or delay evaluation and treatment of an underlying condition‚ other than SCN‚ causing the neutropenia.

CONTRAINDICATIONS

NEUPOGEN® is contraindicated in patients with known hypersensitivity to E coli-derived proteins‚ Filgrastim‚ or any component of the product.

WARNINGS

Allergic Reactions

Allergic-type reactions occurring on initial or subsequent treatment have been reported in less than 1 in 4000 patients treated with NEUPOGEN®. These have generally been characterized by systemic symptoms involving at least 2 body systems‚ most often skin (rash‚ urticaria‚ facial edema)‚ respiratory (wheezing‚ dyspnea)‚ and cardiovascular (hypotension‚ tachycardia). Some reactions occurred on initial exposure. Reactions tended to occur within the first 30 minutes after administration and appeared to occur more frequently in patients receiving NEUPOGEN® IV. Rapid resolution of symptoms occurred in most cases after administration of antihistamines‚ steroids‚ bronchodilators‚ and/or epinephrine. Symptoms recurred in more than half the patients who were rechallenged.

SPLENIC RUPTURE

SPLENIC RUPTURE, INCLUDING FATAL CASES, HAS BEEN REPORTED FOLLOWING THE ADMINISTRATION OF NEUPOGEN®. INDIVIDUALS RECEIVING NEUPOGEN® WHO REPORT LEFT UPPER ABDOMINAL AND/OR SHOULDER TIP PAIN SHOULD BE EVALUATED FOR AN ENLARGED SPLEEN OR SPLENIC RUPTURE.

Acute Respiratory Distress Syndrome (ARDS)

Acute respiratory distress syndrome (ARDS) has been reported in patients receiving NEUPOGEN®, and is postulated to be secondary to an influx of neutrophils to sites of inflammation in the lungs. Patients receiving NEUPOGEN® who develop fever, lung infiltrates, or respiratory distress should be evaluated for the possibility of ARDS. In the event that ARDS occurs, NEUPOGEN® should be withheld until resolution of ARDS or discontinued. Patients should receive appropriate medical management for this condition.

Alveolar Hemorrhage and Hemoptysis

Alveolar hemorrhage manifesting as pulmonary infiltrates and hemoptysis requiring hospitalization has been reported in healthy donors undergoing peripheral blood progenitor cell (PBPC) mobilization. Hemoptysis resolved with discontinuation of NEUPOGEN®. The use of NEUPOGEN® for PBPC mobilization in healthy donors is not an approved indication.

Sickle Cell Disorders

Severe sickle cell crises, in some cases resulting in death, have been associated with the use of NEUPOGEN® in patients with sickle cell disorders. Only physicians qualified by specialized training or experience in the treatment of patients with sickle cell disorders should prescribe NEUPOGEN® for such patients, and only after careful consideration of the potential risks and benefits.

Patients With Severe Chronic Neutropenia

The safety and efficacy of NEUPOGEN® in the treatment of neutropenia due to other hematopoietic disorders (eg‚ myelodysplastic syndrome [MDS]) have not been established. Care should be taken to confirm the diagnosis of SCN before initiating NEUPOGEN® therapy.

MDS and AML have been reported to occur in the natural history of congenital neutropenia without cytokine therapy.^17 Cytogenetic abnormalities, transformation to MDS, and AML have also been observed in patients treated with NEUPOGEN® for SCN. Based on available data including a postmarketing surveillance study, the risk of developing MDS and AML appears to be confined to the subset of patients with congenital neutropenia (see ADVERSE REACTIONS). Abnormal cytogenetics and MDS have been associated with the eventual development of myeloid leukemia. The effect of NEUPOGEN® on the development of abnormal cytogenetics and the effect of continued NEUPOGEN® administration in patients with abnormal cytogenetics or MDS are unknown. If a patient with SCN develops abnormal cytogenetics or myelodysplasia‚ the risks and benefits of continuing NEUPOGEN® should be carefully considered.

PRECAUTIONS

General Simultaneous Use With Chemotherapy and Radiation Therapy

The safety and efficacy of NEUPOGEN® given simultaneously with cytotoxic chemotherapy have not been established. Because of the potential sensitivity of rapidly dividing myeloid cells to cytotoxic chemotherapy‚ do not use NEUPOGEN® in the period 24 hours before through 24 hours after the administration of cytotoxic chemotherapy (see DOSAGE AND ADMINISTRATION).

The efficacy of NEUPOGEN® has not been evaluated in patients receiving chemotherapy associated with delayed myelosuppression (eg, nitrosoureas) or with mitomycin C or with myelosuppressive doses of antimetabolites such as 5-fluorouracil.

The safety and efficacy of NEUPOGEN® have not been evaluated in patients receiving concurrent radiation therapy. Simultaneous use of NEUPOGEN® with chemotherapy and radiation therapy should be avoided.

Potential Effect on Malignant Cells

NEUPOGEN® is a growth factor that primarily stimulates neutrophils. However‚ the possibility that NEUPOGEN® can act as a growth factor for any tumor type cannot be excluded. In a randomized study evaluating the effects of NEUPOGEN® versus placebo in patients undergoing remission induction for AML, there was no significant difference in remission rate, disease-free, or overall survival (see CLINICAL EXPERIENCE).

The safety of NEUPOGEN® in chronic myeloid leukemia (CML) and myelodysplasia has not been established.

When NEUPOGEN® is used to mobilize PBPC‚ tumor cells may be released from the marrow and subsequently collected in the leukapheresis product. The effect of reinfusion of tumor cells has not been well studied‚ and the limited data available are inconclusive.

Leukocytosis Cancer Patients Receiving Myelosuppressive Chemotherapy

White blood cell counts of 100‚000/mm^3 or greater were observed in approximately 2% of patients receiving NEUPOGEN® at doses above 5 mcg/kg/day. There were no reports of adverse events associated with this degree of leukocytosis. In order to avoid the potential complications of excessive leukocytosis‚ a CBC is recommended twice per week during NEUPOGEN® therapy (see LABORATORY MONITORING).

Premature Discontinuation of NEUPOGEN® Therapy Cancer Patients Receiving Myelosuppressive Chemotherapy

A transient increase in neutrophil counts is typically seen 1 to 2 days after initiation of NEUPOGEN® therapy. However‚ for a sustained therapeutic response‚ NEUPOGEN® therapy should be continued following chemotherapy until the post nadir ANC reaches 10‚000/mm^3. Therefore‚ the premature discontinuation of NEUPOGEN® therapy‚ prior to the time of recovery from the expected neutrophil nadir‚ is generally not recommended (see DOSAGE AND ADMINISTRATION).

Immunogenicity

As with all therapeutic proteins, there is a potential for immunogenicity. The incidence of antibody development in patients receiving NEUPOGEN® has not been adequately determined. While available data suggest that a small proportion of patients developed binding antibodies to Filgrastim, the nature and specificity of these antibodies has not been adequately studied. In clinical studies comparing NEUPOGEN® and Neulasta®, the incidence of antibodies binding to NEUPOGEN® was 3% (11/333). In these 11 patients, no evidence of a neutralizing response was observed using a cell-based bioassay. The detection of antibody formation is highly dependent on the sensitivity and specificity of the assay, and the observed incidence of antibody positivity in an assay may be influenced by several factors including timing of sampling, sample handling, concomitant medications, and underlying disease. Therefore, comparison of the incidence of antibodies to NEUPOGEN® with the incidence of antibodies to other products may be misleading.

Cytopenias resulting from an antibody response to exogenous growth factors have been reported on rare occasions in patients treated with other recombinant growth factors. There is a theoretical possibility that an antibody directed against Filgrastim may cross-react with endogenous G-CSF, resulting in immune-mediated neutropenia; however, this has not been reported in clinical studies or in post-marketing experience. Patients who develop hypersensitivity to Filgrastim (NEUPOGEN®) may have allergic or hypersensitivity reactions to other E coli-derived proteins.

Cutaneous Vasculitis

Cutaneous vasculitis has been reported in patients treated with NEUPOGEN®. In most cases‚ the severity of cutaneous vasculitis was moderate or severe. Most of the reports involved patients with SCN receiving long-term NEUPOGEN® therapy. Symptoms of vasculitis generally developed simultaneously with an increase in the ANC and abated when the ANC decreased. Many patients were able to continue NEUPOGEN® at a reduced dose.

Information for Patients and Caregivers

Patients should be referred to the “Information for Patients and Caregivers” labeling included with the package insert in each dispensing pack of NEUPOGEN® vials or NEUPOGEN® prefilled syringes. The “Information for Patients and Caregivers” labeling provides information about neutrophils and neutropenia and the safety and efficacy of NEUPOGEN®. It is not intended to be a disclosure of all known or possible effects.

Laboratory Monitoring Cancer Patients Receiving Myelosuppressive Chemotherapy

A CBC and platelet count should be obtained prior to chemotherapy‚ and at regular intervals (twice per week) during NEUPOGEN® therapy. Following cytotoxic chemotherapy‚ the neutrophil nadir occurred earlier during cycles when NEUPOGEN® was administered‚ and WBC differentials demonstrated a left shift‚ including the appearance of promyelocytes and myeloblasts. In addition‚ the duration of severe neutropenia was reduced‚ and was followed by an accelerated recovery in the neutrophil counts.

Cancer Patients Receiving Bone Marrow Transplant

Frequent CBCs and platelet counts are recommended (at least 3 times per week) following marrow transplantation.

Patients With Severe Chronic Neutropenia

During the initial 4 weeks of NEUPOGEN® therapy and during the 2 weeks following any dose adjustment‚ a CBC with differential and platelet count should be performed twice weekly. Once a patient is clinically stable‚ a CBC with differential and platelet count should be performed monthly during the first year of treatment. Thereafter, if clinically stable, routine monitoring with regular CBCs (ie, as clinically indicated but at least quarterly) is recommended. Additionally, for those patients with congenital neutropenia, annual bone marrow and cytogenetic evaluations should be performed throughout the duration of treatment (see WARNINGS, ADVERSE REACTIONS).

In clinical trials‚ the following laboratory results were observed:

- Cyclic fluctuations in the neutrophil counts were frequently observed in patients with congenital or idiopathic neutropenia after initiation of NEUPOGEN® therapy.
- Platelet counts were generally at the upper limits of normal prior to NEUPOGEN® therapy. With NEUPOGEN® therapy‚ platelet counts decreased but usually remained within normal limits (see ADVERSE REACTIONS).
- Early myeloid forms were noted in peripheral blood in most patients‚ including the appearance of metamyelocytes and myelocytes. Promyelocytes and myeloblasts were noted in some patients.
- Relative increases were occasionally noted in the number of circulating eosinophils and basophils. No consistent increases were observed with NEUPOGEN® therapy.
- As in other trials‚ increases were observed in serum uric acid‚ lactic dehydrogenase‚ and serum alkaline phosphatase.

Drug Interaction

Drug interactions between NEUPOGEN® and other drugs have not been fully evaluated. Drugs which may potentiate the release of neutrophils‚ such as lithium‚ should be used with caution.

Increased hematopoietic activity of the bone marrow in response to growth factor therapy has been associated with transient positive bone imaging changes. This should be considered when interpreting bone-imaging results.

Carcinogenesis, Mutagenesis, Impairment of Fertility

The carcinogenic potential of NEUPOGEN® has not been studied. NEUPOGEN® failed to induce bacterial gene mutations in either the presence or absence of a drug metabolizing enzyme system. NEUPOGEN® had no observed effect on the fertility of male or female rats‚ or on gestation at doses up to 500 mcg/kg.

Pregnancy Category C

NEUPOGEN® has been shown to have adverse effects in pregnant rabbits when given in doses 2 to 10 times the human dose. Since there are no adequate and well-controlled studies in pregnant women, the effect, if any, of NEUPOGEN® on the developing fetus or the reproductive capacity of the mother is unknown. However, the scientific literature describes transplacental passage of NEUPOGEN® when administered to pregnant rats during the latter part of gestation^18 and apparent transplacental passage of NEUPOGEN® when administered to pregnant humans by ≤ 30 hours prior to preterm delivery (≤ 30 weeks gestation).^19 NEUPOGEN® should be used during pregnancy only if the potential benefit justifies the potential risk to the fetus.

In rabbits‚ increased abortion and embryolethality were observed in animals treated with NEUPOGEN® at 80 mcg/kg/day. NEUPOGEN® administered to pregnant rabbits at doses of 80 mcg/kg/day during the period of organogenesis was associated with increased fetal resorption‚ genitourinary bleeding‚ developmental abnormalities‚ decreased body weight‚ live births‚ and food consumption. External abnormalities were not observed in the fetuses of dams treated at 80 mcg/kg/day. Reproductive studies in pregnant rats have shown that NEUPOGEN® was not associated with lethal‚ teratogenic‚ or behavioral effects on fetuses when administered by daily IV injection during the period of organogenesis at dose levels up to 575 mcg/kg/day.

In Segment III studies in rats‚ offspring of dams treated at > 20 mcg/kg/day exhibited a delay in external differentiation (detachment of auricles and descent of testes) and slight growth retardation‚ possibly due to lower body weight of females during rearing and nursing. Offspring of dams treated at 100 mcg/kg/day exhibited decreased body weights at birth‚ and a slightly reduced 4-day survival rate.

Nursing Mothers

It is not known whether NEUPOGEN® is excreted in human milk. Because many drugs are excreted in human milk‚ caution should be exercised if NEUPOGEN® is administered to a nursing woman.

Pediatric Use

In a phase 3 study to assess the safety and efficacy of NEUPOGEN® in the treatment of SCN, 120 patients with a median age of 12 years were studied. Of the 120 patients, 12 were infants (1 month to 2 years of age), 47 were children (2 to 12 years of age), and 9 were adolescents (12 to 16 years of age). Additional information is available from a SCN postmarketing surveillance study, which includes long-term follow-up of patients in the clinical studies and information from additional patients who entered directly into the postmarketing surveillance study. Of the 531 patients in the surveillance study as of 31 December 1997, 32 were infants, 200 were children, and 68 were adolescents (see CLINICAL EXPERIENCE, INDICATIONS AND USAGE, LABORATORY MONITORING, DOSAGE AND ADMINISTRATION).

Pediatric patients with congenital types of neutropenia (Kostmann’s syndrome, congenital agranulocytosis, or Schwachman-Diamond syndrome) have developed cytogenetic abnormalities and have undergone transformation to MDS and AML while receiving chronic NEUPOGEN® treatment. The relationship of these events to NEUPOGEN® administration is unknown (see WARNINGS, ADVERSE REACTIONS).

Long-term follow-up data from the postmarketing surveillance study suggest that height and weight are not adversely affected in patients who received up to 5 years of NEUPOGEN® treatment. Limited data from patients who were followed in the phase 3 study for 1.5 years did not suggest alterations in sexual maturation or endocrine function.

The safety and efficacy in neonates and patients with autoimmune neutropenia of infancy have not been established.

In the cancer setting‚ 12 pediatric patients with neuroblastoma have received up to 6 cycles of cyclophosphamide‚ cisplatin‚ doxorubicin‚ and etoposide chemotherapy concurrently with NEUPOGEN®; in this population‚ NEUPOGEN® was well tolerated. There was one report of palpable splenomegaly associated with NEUPOGEN® therapy; however‚ the only consistently reported adverse event was musculoskeletal pain‚ which is no different from the experience in the adult population.

Geriatric Use

Among 855 subjects enrolled in 3 randomized, placebo-controlled trials of NEUPOGEN® use following myelosuppressive chemotherapy, there were 232 subjects age 65 or older, and 22 subjects age 75 or older. No overall differences in safety or effectiveness were observed between these subjects and younger subjects, and other clinical experience has not identified differences in the responses between elderly and younger patients.

Clinical studies of NEUPOGEN® in other approved indications (ie, bone marrow transplant recipients, PBPC mobilization, and SCN) did not include sufficient numbers of subjects aged 65 and older to determine whether elderly subjects respond differently from younger subjects.

ADVERSE REACTIONS

Clinical Trial Experience Cancer Patients Receiving Myelosuppressive Chemotherapy

In clinical trials involving over 350 patients receiving NEUPOGEN® following nonmyeloablative cytotoxic chemotherapy‚ most adverse experiences were the sequelae of the underlying malignancy or cytotoxic chemotherapy. In all phase 2 and 3 trials‚ medullary bone pain‚ reported in 24% of patients‚ was the only consistently observed adverse reaction attributed to NEUPOGEN® therapy. This bone pain was generally reported to be of mild-to-moderate severity‚ and could be controlled in most patients with non-narcotic analgesics; infrequently‚ bone pain was severe enough to require narcotic analgesics. Bone pain was reported more frequently in patients treated with higher doses (20 to 100 mcg/kg/day) administered IV‚ and less frequently in patients treated with lower SC doses of NEUPOGEN® (3 to 10 mcg/kg/day).

In the randomized‚ double-blind‚ placebo-controlled trial of NEUPOGEN® therapy following combination chemotherapy in patients (n = 207) with small cell lung cancer‚ the following adverse events were reported during blinded cycles of study medication (placebo or NEUPOGEN® at 4 to 8 mcg/kg/day). Events are reported as exposure-adjusted since patients remained on double-blind NEUPOGEN® a median of 3 cycles versus 1 cycle for placebo.

 | % of Blinded Cycles With Events
 | NEUPOGEN® N = 384 Patient Cycles | Placebo N = 257 Patient Cycles
Event
Nausea/Vomiting | 57 | 64
Skeletal Pain | 22 | 11
Alopecia | 18 | 27
Diarrhea | 14 | 23
Neutropenic Fever | 13 | 35
Mucositis | 12 | 20
Fever | 12 | 11
Fatigue | 11 | 16
Anorexia | 9 | 11
Dyspnea | 9 | 11
Headache | 7 | 9
Cough | 6 | 8
Skin Rash | 6 | 9
Chest Pain | 5 | 6
Generalized Weakness | 4 | 7
Sore Throat | 4 | 9
Stomatitis | 5 | 10
Constipation | 5 | 10
Pain (Unspecified) | 2 | 7

In this study‚ there were no serious‚ life-threatening‚ or fatal adverse reactions attributed to NEUPOGEN® therapy. Specifically‚ there were no reports of flu-like symptoms‚ pleuritis‚ pericarditis‚ or other major systemic reactions to NEUPOGEN®.

Spontaneously reversible elevations in uric acid‚ lactate dehydrogenase‚ and alkaline phosphatase occurred in 27% to 58% of 98 patients receiving blinded NEUPOGEN® therapy following cytotoxic chemotherapy; increases were generally mild-to-moderate. Transient decreases in blood pressure (less than 90/60 mmHg)‚ which did not require clinical treatment‚ were reported in 7 of 176 patients in phase 3 clinical studies following administration of NEUPOGEN®. Cardiac events (myocardial infarctions‚ arrhythmias) have been reported in 11 of 375 cancer patients receiving NEUPOGEN® in clinical studies; the relationship to NEUPOGEN® therapy is unknown. No evidence of interaction of NEUPOGEN® with other drugs was observed in the course of clinical trials (see PRECAUTIONS).

There has been no evidence for the development of antibodies or of a blunted or diminished response to NEUPOGEN® in treated patients‚ including those receiving NEUPOGEN® daily for almost 2 years.

Patients With Acute Myeloid Leukemia

In a randomized phase 3 clinical trial, 259 patients received NEUPOGEN® and 262 patients received placebo postchemotherapy. Overall, the frequency of all reported adverse events was similar in both the NEUPOGEN® and placebo groups (83% vs 82% in Induction 1; 61% vs 64% in Consolidation 1). Adverse events reported more frequently in the NEUPOGEN®-treated group included: petechiae (17% vs 14%), epistaxis (9% vs 5%), and transfusion reactions (10% vs 5%). There were no significant differences in the frequency of these events.

There were a similar number of deaths in each treatment group during induction (25 NEUPOGEN® vs 27 placebo). The primary causes of death included infection (9 vs 18), persistent leukemia (7 vs 5), and hemorrhage (6 vs 3). Of the hemorrhagic deaths, 5 cerebral hemorrhages were reported in the NEUPOGEN® group and 1 in the placebo group. Other serious nonfatal hemorrhagic events were reported in the respiratory tract (4 vs 1), skin (4 vs 4), gastrointestinal tract (2 vs 2), urinary tract (1 vs 1), ocular (1 vs 0), and other nonspecific sites (2 vs 1). While 19 (7%) patients in the NEUPOGEN® group and 5 (2%) patients in the placebo group experienced severe or fatal hemorrhagic events, overall, hemorrhagic adverse events were reported at a similar frequency in both groups (40% vs 38%). The time to transfusion-independent platelet recovery and the number of days of platelet transfusions were similar in both groups.

Cancer Patients Receiving Bone Marrow Transplant

In clinical trials‚ the reported adverse effects were those typically seen in patients receiving intensive chemotherapy followed by bone marrow transplant (BMT). The most common events reported in both control and treatment groups included stomatitis, nausea, and vomiting‚ generally of mild-to-moderate severity and were considered unrelated to NEUPOGEN®. In the randomized studies of BMT involving 167 patients who received study drug‚ the following events occurred more frequently in patients treated with Filgrastim than in controls: nausea (10% vs 4%)‚ vomiting (7% vs 3%)‚ hypertension (4% vs 0%)‚ rash (12% vs 10%)‚ and peritonitis (2% vs 0%). None of these events were reported by the investigator to be related to NEUPOGEN®. One event of erythema nodosum was reported moderate in severity and possibly related to NEUPOGEN®.

Generally‚ adverse events observed in nonrandomized studies were similar to those seen in randomized studies‚ occurred in a minority of patients, and were of mild-to-moderate severity. In one study (n = 45)‚ 3 serious adverse events reported by the investigator were considered possibly related to NEUPOGEN®. These included 2 events of renal insufficiency and 1 event of capillary leak syndrome. The relationship of these events to NEUPOGEN® remains unclear since they occurred in patients with culture-proven infection with clinical sepsis who were receiving potentially nephrotoxic antibacterial and antifungal therapy.

Cancer Patients Undergoing Peripheral Blood Progenitor Cell Collection and Therapy

In clinical trials‚ 126 patients received NEUPOGEN® for PBPC mobilization. In this setting‚ NEUPOGEN® was generally well tolerated. Adverse events related to NEUPOGEN® consisted primarily of mild-to-moderate musculoskeletal symptoms‚ reported in 44% of patients. These symptoms were predominantly events of medullary bone pain (33%). Headache was reported related to NEUPOGEN® in 7% of patients. Transient increases in alkaline phosphatase related to NEUPOGEN® were reported in 21% of the patients who had serum chemistries measured; most were mild-to-moderate.

All patients had increases in neutrophil counts during mobilization‚ consistent with the biological effects of NEUPOGEN®. Two patients had a WBC count greater than 100‚000/mm^3. No sequelae were associated with any grade of leukocytosis.

Sixty-five percent of patients had mild-to-moderate anemia and 97% of patients had decreases in platelet counts; 5 patients (out of 126) had decreased platelet counts to less than 50‚000/mm^3. Anemia and thrombocytopenia have been reported to be related to leukapheresis; however‚ the possibility that NEUPOGEN® mobilization may contribute to anemia or thrombocytopenia has not been ruled out.

Patients With Severe Chronic Neutropenia

Mild-to-moderate bone pain was reported in approximately 33% of patients in clinical trials. This symptom was readily controlled with non-narcotic analgesics. Generalized musculoskeletal pain was also noted in higher frequency in patients treated with NEUPOGEN®. Palpable splenomegaly was observed in approximately 30% of patients. Abdominal or flank pain was seen infrequently, and thrombocytopenia (less than 50‚000/mm^3) was noted in 12% of patients with palpable spleens. Fewer than 3% of all patients underwent splenectomy‚ and most of these had a prestudy history of splenomegaly. Fewer than 6% of patients had thrombocytopenia (less than 50‚000/mm^3) during NEUPOGEN® therapy‚ most of whom had a pre-existing history of thrombocytopenia. In most cases‚ thrombocytopenia was managed by NEUPOGEN® dose reduction or interruption. An additional 5% of patients had platelet counts between 50‚000 and 100‚000/mm^3. There were no associated serious hemorrhagic sequelae in these patients. Epistaxis was noted in 15% of patients treated with NEUPOGEN®‚ but was associated with thrombocytopenia in 2% of patients. Anemia was reported in approximately 10% of patients‚ but in most cases appeared to be related to frequent diagnostic phlebotomy‚ chronic illness, or concomitant medications. Other adverse events infrequently observed and possibly related to NEUPOGEN® therapy were: injection site reaction‚ rash‚ hepatomegaly‚ arthralgia‚ osteoporosis‚ cutaneous vasculitis‚ hematuria/proteinuria‚ alopecia‚ and exacerbation of some pre-existing skin disorders (eg‚ psoriasis).

Cytogenetic abnormalities, transformation to MDS, and AML have been observed in patients treated with NEUPOGEN® for SCN (see WARNINGS, PRECAUTIONS: Pediatric Use). As of 31 December 1997, data were available from a postmarketing surveillance study of 531 SCN patients with an average follow-up of 4.0 years. Based on analysis of these data, the risk of developing MDS and AML appears to be confined to the subset of patients with congenital neutropenia. A life-table analysis of these data revealed that the cumulative risk of developing leukemia or MDS by the end of the 8th year of NEUPOGEN® treatment in a patient with congenital neutropenia was 16.5% (95% C.I. = 9.8%, 23.3%); this represents an annual rate of approximately 2%. Cytogenetic abnormalities, most commonly involving chromosome 7, have been reported in patients treated with NEUPOGEN® who had previously documented normal cytogenetics. It is unknown whether the development of cytogenetic abnormalities, MDS, or AML is related to chronic daily NEUPOGEN® administration or to the natural history of congenital neutropenia. It is also unknown if the rate of conversion in patients who have not received NEUPOGEN® is different from that of patients who have received NEUPOGEN®. Routine monitoring through regular CBCs is recommended for all SCN patients. Additionally, annual bone marrow and cytogenetic evaluations are recommended in all patients with congenital neutropenia (see LABORATORY MONITORING).

Postmarketing Experience

The following adverse reactions have been identified during postapproval of NEUPOGEN®. Because these reactions are reported voluntarily from a population of uncertain size, it is not always possible to reliably estimate their frequency or establish a causal relationship to drug exposure.

- splenic rupture (see WARNINGS: Splenic Rupture)
- acute respiratory distress syndrome (ARDS) (see WARNINGS: Acute Respiratory Distress Syndrome)
- alveolar hemorrhage and hemoptysis (see WARNINGS: Alveolar Hemorrhage and Hemoptysis)
- sickle cell crisis (see WARNINGS: Sickle Cell Disorders)
- cutaneous vasculitis (see PRECAUTIONS: Cutaneous Vasculitis)
- Sweet’s syndrome (acute febrile neutrophilic dermatosis)

OVERDOSAGE

In cancer patients receiving NEUPOGEN® as an adjunct to myelosuppressive chemotherapy‚ it is recommended‚ to avoid the potential risks of excessive leukocytosis‚ that NEUPOGEN® therapy be discontinued if the ANC surpasses 10‚000/mm^3 after the chemotherapy-induced ANC nadir has occurred. Doses of NEUPOGEN® that increase the ANC beyond 10‚000/mm^3 may not result in any additional clinical benefit.

The maximum tolerated dose of NEUPOGEN® has not been determined. Efficacy was demonstrated at doses of 4 to 8 mcg/kg/day in the phase 3 study of nonmyeloablative chemotherapy. Patients in the BMT studies received up to 138 mcg/kg/day without toxic effects‚ although there was a flattening of the dose response curve above daily doses of greater than 10 mcg/kg/day.

In NEUPOGEN® clinical trials of cancer patients receiving myelosuppressive chemotherapy‚ WBC counts > 100‚000/mm^3 have been reported in less than 5% of patients‚ but were not associated with any reported adverse clinical effects.

In cancer patients receiving myelosuppressive chemotherapy‚ discontinuation of NEUPOGEN® therapy usually results in a 50% decrease in circulating neutrophils within 1 to 2 days‚ with a return to pretreatment levels in 1 to 7 days.

DOSAGE AND ADMINISTRATION

NEUPOGEN® is supplied in either vials or in prefilled syringes with UltraSafe® Needle Guards. Following administration of NEUPOGEN® from the prefilled syringe, the UltraSafe® Needle Guard should be activated to prevent accidental needle sticks. To activate the UltraSafe® Needle Guard, place your hands behind the needle, grasp the guard with one hand, and slide the guard forward until the needle is completely covered and the guard clicks into place. NOTE: If an audible click is not heard, the needle guard may not be completely activated. The prefilled syringe should be disposed of by placing the entire prefilled syringe with guard activated into an approved puncture-proof container.

Cancer Patients Receiving Myelosuppressive Chemotherapy

The recommended starting dose of NEUPOGEN® is 5 mcg/kg/day‚ administered as a single daily injection by SC bolus injection‚ by short IV infusion (15 to 30 minutes)‚ or by continuous SC or continuous IV infusion. A CBC and platelet count should be obtained before instituting NEUPOGEN® therapy‚ and monitored twice weekly during therapy. Doses may be increased in increments of 5 mcg/kg for each chemotherapy cycle‚ according to the duration and severity of the ANC nadir.

NEUPOGEN® should be administered no earlier than 24 hours after the administration of cytotoxic chemotherapy. NEUPOGEN® should not be administered in the period 24 hours before the administration of chemotherapy (see PRECAUTIONS). NEUPOGEN® should be administered daily for up to 2 weeks‚ until the ANC has reached 10‚000/mm^3 following the expected chemotherapy-induced neutrophil nadir. The duration of NEUPOGEN® therapy needed to attenuate chemotherapy-induced neutropenia may be dependent on the myelosuppressive potential of the chemotherapy regimen employed. NEUPOGEN® therapy should be discontinued if the ANC surpasses 10‚000/mm^3 after the expected chemotherapy-induced neutrophil nadir (see PRECAUTIONS). In phase 3 trials‚ efficacy was observed at doses of 4 to 8 mcg/kg/day.

Cancer Patients Receiving Bone Marrow Transplant

The recommended dose of NEUPOGEN® following BMT is 10 mcg/kg/day given as an IV infusion of 4 or 24 hours‚ or as a continuous 24-hour SC infusion. For patients receiving BMT‚ the first dose of NEUPOGEN® should be administered at least 24 hours after cytotoxic chemotherapy and at least 24 hours after bone marrow infusion.

During the period of neutrophil recovery‚ the daily dose of NEUPOGEN® should be titrated against the neutrophil response as follows:

Absolute Neutrophil Count | NEUPOGEN® Dose Adjustment
When ANC greater than 1000/mm^3 for
3 consecutive days | Reduce to 5 mcg/kg/day*
then:
If ANC remains greater than 1000/mm^3
for 3 more consecutive days | Discontinue NEUPOGEN®
then:
If ANC decreases to less than 1000/mm^3 | Resume at 5 mcg/kg/day

* If ANC decreases to less than 1000/mm^3 at any time during the 5 mcg/kg/day administration‚ NEUPOGEN® should be increased to 10 mcg/kg/day‚ and the above steps should then be followed.

Peripheral Blood Progenitor Cell Collection and Therapy in Cancer Patients

The recommended dose of NEUPOGEN® for the mobilization of PBPC is 10 mcg/kg/day SC‚ either as a bolus or a continuous infusion. It is recommended that NEUPOGEN® be given for at least 4 days before the first leukapheresis procedure and continued until the last leukapheresis. Although the optimal duration of NEUPOGEN® administration and leukapheresis schedule have not been established‚ administration of NEUPOGEN® for 6 to 7 days with leukaphereses on days 5‚ 6‚ and 7 was found to be safe and effective (see CLINICAL EXPERIENCE for schedules used in clinical trials). Neutrophil counts should be monitored after 4 days of NEUPOGEN®, and NEUPOGEN® dose modification should be considered for those patients who develop a WBC count greater than 100‚000/mm^3.

In all clinical trials of NEUPOGEN® for the mobilization of PBPC‚ NEUPOGEN® was also administered after reinfusion of the collected cells (see CLINICAL EXPERIENCE).

Patients With Severe Chronic Neutropenia

NEUPOGEN® should be administered to those patients in whom a diagnosis of congenital‚ cyclic‚ or idiopathic neutropenia has been definitively confirmed. Other diseases associated with neutropenia should be ruled out.

Starting Dose:

Congenital Neutropenia: The recommended daily starting dose is 6 mcg/kg BID SC every day.

Idiopathic or Cyclic Neutropenia: The recommended daily starting dose is 5 mcg/kg as a single injection SC every day.

Dose Adjustments:

Chronic daily administration is required to maintain clinical benefit. Absolute neutrophil count should not be used as the sole indication of efficacy. The dose should be individually adjusted based on the patients’ clinical course as well as ANC. In the SCN postmarketing surveillance study, the reported median daily doses of NEUPOGEN® were: 6.0 mcg/kg (congenital neutropenia), 2.1 mcg/kg (cyclic neutropenia), and 1.2 mcg/kg (idiopathic neutropenia). In rare instances, patients with congenital neutropenia have required doses of NEUPOGEN® greater than or equal to 100 mcg/kg/day.

Dilution

If required‚ NEUPOGEN® may be diluted in 5% dextrose. NEUPOGEN® diluted to concentrations between 5 and 15 mcg/mL should be protected from adsorption to plastic materials by the addition of Albumin (Human) to a final concentration of 2 mg/mL. When diluted in 5% dextrose or 5% dextrose plus Albumin (Human)‚ NEUPOGEN® is compatible with glass bottles‚ PVC and polyolefin IV bags‚ and polypropylene syringes.

Dilution of NEUPOGEN® to a final concentration of less than 5 mcg/mL is not recommended at any time. Do not dilute with saline at any time; product may precipitate.

Storage

NEUPOGEN® should be stored in the refrigerator at 2° to 8°C (36° to 46°F). Avoid shaking. Prior to injection‚ NEUPOGEN® may be allowed to reach room temperature for a maximum of 24 hours. Any vial or prefilled syringe left at room temperature for greater than 24 hours should be discarded. Parenteral drug products should be inspected visually for particulate matter and discoloration prior to administration‚ whenever solution and container permit; if particulates or discoloration are observed‚ the container should not be used.

HOW SUPPLIED

NEUPOGEN®: Use only one dose per vial; do not re-enter the vial. Discard unused portions. Do not save unused drug for later administration.

Use only one dose per prefilled syringe. Discard unused portions. Do not save unused drug for later administration.

Vials

Single-dose‚ preservative-free vials containing 300 mcg (1 mL) of Filgrastim (300 mcg/mL). 1 Vial (NDC 54868-2522-0); Dispensing packs of 10 (NDC 54868-2522-1).

Prefilled Syringes (SingleJect®)

Single-dose‚ preservative-free, prefilled syringes with 27 gauge, ½ inch needles with an UltraSafe® Needle Guard, containing 300 mcg (0.5 mL) of Filgrastim (600 mcg/mL). Dispensing packs of 10 (NDC 54868-5020-0).

Single-dose‚ preservative-free, prefilled syringes with 27 gauge, ½ inch needles with an UltraSafe® Needle Guard, containing 480 mcg (0.8 mL) of Filgrastim (600 mcg/mL). Dispensing packs of 10 (NDC 54868-3050-0).

The needle cover of the prefilled syringe contains dry natural rubber (a derivative of latex).

NEUPOGEN® should be stored at 2° to 8°C (36° to 46°F). Avoid shaking.

REFERENCES

1. Zsebo KM‚ Cohen AM‚ Murdock DC‚ et al. Recombinant human granulocyte colony-stimulating factor: Molecular and biological characterization. Immunobiol. 1986;172:175-184.
2. Welte K‚ Bonilla MA‚ Gillio AP‚ et al. Recombinant human G-CSF: Effects on hematopoiesis in normal and cyclophosphamide treated primates. J Exp Med. 1987;165:941-948.
3. Duhrsen U‚ Villeval JL‚ Boyd J‚ et al. Effects of recombinant human granulocyte colony-stimulating factor on hematopoietic progenitor cells in cancer patients. Blood. 1988;72:2074-2081.
4. Souza LM‚ Boone TC‚ Gabrilove J‚ et al. Recombinant human granulocyte colony-stimulating factor: Effects on normal and leukemic myeloid cells. Science. 1986;232:61-65.
5. Weisbart RH‚ Kacena A‚ Schuh A‚ Golde DW. GM-CSF induces human neutrophil IgA-mediated phagocytosis by an IgA Fc receptor activation mechanism. Nature. 1988;332:647-648.
6. Kitagawa S‚ Yuo A‚ Souza LM‚ Saito M‚ Miura Y‚ Takaku F. Recombinant human granulocyte colony-stimulating factor enhances superoxide release in human granulocytes stimulated by chemotactic peptide. Biochem Biophys Res Commun. 1987;1443:1146.
7. Glaspy JA‚ Baldwin GC‚ Robertson PA‚ et al. Therapy for neutropenia in hairy cell leukemia with recombinant human granulocyte colony-stimulating factor. Ann Int Med. 1988;109:789-795.
8. Yuo A‚ Kitagawa S‚ Ohsaka A‚ et al. Recombinant human granulocyte colony-stimulating factor as an activator of human granulocytes: Potentiation of responses triggered by receptor-mediated agonists and stimulation of C3bi receptor expression and adherence. Blood. 1989;74:2144-2149.
9. Gabrilove JL‚ Jakubowski A‚ Fain K‚ et al. Phase I study of granulocyte colony-stimulating factor in patients with transitional cell carcinoma of the urothelium. J Clin Invest. 1988;82:1454-1461.
10. Morstyn G‚ Souza L‚ Keech J‚ et al. Effect of granulocyte colony-stimulating factor on neutropenia induced by cytotoxic chemotherapy. Lancet. 1988;1:667-672.
11. Bronchud MH‚ Scarffe JH‚ Thatcher N‚ et al. Phase I/II study of recombinant human granulocyte colony-stimulating factor in patients receiving intensive chemotherapy for small cell lung cancer. Br J Cancer. 1987;56:809-813.
12. Gabrilove JL‚ Jakubowski A‚ Scher H‚ et al. Effect of granulocyte colony-stimulating factor on neutropenia and associated morbidity due to chemotherapy for transitional cell carcinoma of the urothelium. N Engl J Med. 1988;318:1414-1422.
13. Neidhart J‚ Mangalik A‚ Kohler W‚ et al. Granulocyte colony-stimulating factor stimulates recovery of granulocytes in patients receiving dose-intensive chemotherapy without bone-marrow transplantation. J Clin Oncol. 1989;7:1685-1691.
14. Bronchud MH‚ Howell A‚ Crowther D‚ et al. The use of granulocyte colony-stimulating factor to increase the intensity of treatment with doxorubicin in patients with advanced breast and ovarian cancer. Br J Cancer. 1989;60:121-128.
15. Heil G, Hoelzer D, Sanz MA, et al. A randomized, double-blind, placebo-controlled, phase III study of Filgrastim in remission induction and consolidation therapy for adults with de novo Acute Myeloid Leukemia. Blood. 1997;90:4710-4718.
16. Dale DC‚ Bonilla MA‚ Davis MW‚ et al. A randomized controlled phase III trial of recombinant human granulocyte colony-stimulating factor (Filgrastim) for treatment of severe chronic neutropenia. Blood. 1993;81:2496-2502.
17. Schroeder TM and Kurth R. Spontaneous chromosomal breakage and high incidence of leukemia in inherited disease. Blood. 1971;37:96-112.
18. Medlock ES, Kaplan DL, Cecchini M, Ulich TR, del Castillo J, Andresen J. Granulocyte colony-stimulating factor crosses the placenta and stimulates fetal rat granulopoiesis. Blood. 1993;81:916-922.
19. Calhoun DA, Rosa C, Christensen RD. Transplacental passage of recombinant human granulocyte colony-stimulating factor in women with an imminent preterm delivery. Am J Obstet Gynecol. 1996;174:1306-1311.

This product and its use are covered by the following US Patent Nos.: 4,810,643; 4,999,291; 5,582,823; 5,580,755.

[AMGEN LOGO]

Manufactured by:

Amgen Manufacturing, Limited,

a subsidiary of Amgen Inc.
One Amgen Center Drive
Thousand Oaks, California 91320-1799

3xxxxxx

© 1991-2007 Amgen Inc. All rights reserved.

v.20.2 - Issue Date: 09/2007

PATIENT COUNSELING INFORMATION

NEUPOGEN®
(Filgrastim)
Information for Patients and Caregivers

This patient package insert provides information and instructions for people who will be receiving NEUPOGEN® and their caregivers. This patient package insert does not tell you everything about NEUPOGEN®. You should discuss any questions you have about treatment with NEUPOGEN® with your doctor.

What is NEUPOGEN®?

NEUPOGEN® is a man-made form of granulocyte colony-stimulating factor (G-CSF), which is made using the bacteria E coli. G-CSF is a substance naturally produced by the body. It stimulates the growth of neutrophils (nu-tro-fils), a type of white blood cell important in the body’s fight against infection.

What is NEUPOGEN® used for?

NEUPOGEN® is used to treat neutropenia (nu-tro-peen-ee-ah), a condition where the body makes too few neutrophils. Neutropenia may be a long-standing condition where your body does not make enough neutrophils, or it may be caused by drugs used to treat cancer. In some cases, your body may make enough neutrophils, but as part of your treatment for cancer, your doctor may want to increase the number of certain blood cells (CD34 cells) and collect them. The cells are collected using a process called apheresis (ay-fer-ree-sis). These collected cells are given back to you after you receive very high doses of treatment for cancer to make your blood counts get back to normal more quickly.

How does NEUPOGEN® work?

NEUPOGEN® works by helping your body make more neutrophils. To make sure NEUPOGEN® is working, your doctor will ask that you have regular blood tests to count the number of neutrophils you have. It is important that you follow your doctor’s instructions about getting these tests.

Who should not take NEUPOGEN®?

Do not take NEUPOGEN® if you are:

- Allergic to NEUPOGEN® (Filgrastim) or any of its ingredients. See the end of this leaflet for a list of ingredients in NEUPOGEN®.

- Allergic to other medicines made using the bacteria E coli. Ask your doctor if you are not sure.

What important information do I need to know about taking NEUPOGEN®?

NEUPOGEN® may reduce your chance of getting an infection, but does not prevent all infections. An infection can still happen during the short time when your/your child's neutrophil levels are low. You must be alert and look for some of the common signs or symptoms of infection, such as fever, chills, rash, sore throat, diarrhea, or redness, swelling, or pain around a cut or sore. If you/your child has any of these signs or symptoms during treatment with NEUPOGEN®, tell your doctor or nurse immediately.

There is a possibility that you could have a reaction at an injection site. If there is a lump, swelling, or bruising at an injection site that does not go away, call your doctor.

If you have a sickle cell disorder, make sure that you tell your doctor before you start taking NEUPOGEN®. If you have a sickle cell crisis after getting NEUPOGEN®, tell your doctor right away.

Make sure your doctor knows about all medicines, and herbal or vitamin supplements you are taking before starting NEUPOGEN®. If you are taking lithium you may need more frequent blood tests.

If you/your child are receiving NEUPOGEN® because you are also receiving chemotherapy, the last dose of NEUPOGEN® should be injected at least 24 hours before your next dose of chemotherapy.

There is more information about NEUPOGEN® in the Physician Package Insert. If you have any questions, you should talk to your doctor.

What are possible serious side effects of NEUPOGEN®?

- Spleen Rupture. Your spleen may become enlarged and can rupture while taking NEUPOGEN®. A ruptured spleen can cause death. The spleen is located in the upper left section of your stomach area. Call your doctor right away if you or your child has pain in the left upper stomach area or left shoulder tip area. This pain could mean your or your child’s spleen is enlarged or ruptured.

- Serious Allergic Reactions. NEUPOGEN® can cause serious allergic reactions. These reactions can cause a rash over the whole body, shortness of breath, wheezing, dizziness, swelling around the mouth or eyes, fast pulse, and sweating. If you or your child starts to have any of these symptoms, stop using NEUPOGEN and call your doctor or seek emergency care right away. If you or your child has an allergic reaction during the injection of NEUPOGEN®, stop the injection right away.
- A serious lung problem called acute respiratory distress syndrome (ARDS). Call your doctor or seek emergency care right away if you or your child has shortness of breath, trouble breathing or a fast rate of breathing.

What are the most common side effects of NEUPOGEN®?

The most common side effect you/your child may experience is aching in the bones and muscles. This aching can usually be relieved by taking a non-aspirin pain reliever such as acetaminophen.

Some people experience redness, swelling, or itching at the site of injection. This may be an allergy to the ingredients in NEUPOGEN®, or it may be a local reaction. If you are giving an injection to a child, look for signs of redness, swelling, or itching at the site of injection because they may not be able to tell you they are experiencing a reaction. If you notice any signs of a local reaction, call your doctor.

What about pregnancy or breastfeeding?

NEUPOGEN® has not been studied in pregnant women, and its effects on unborn babies are not known. If you take NEUPOGEN® while you are pregnant, it is possible that small amounts of it may get into your baby’s blood. It is not known if NEUPOGEN® can get into human breast milk.

If you are pregnant, plan to become pregnant, think you may be pregnant, or are breast feeding, you should tell your doctor before using NEUPOGEN®.

How to prepare and give a NEUPOGEN® injection

NEUPOGEN® should be injected at the same time each day. If you miss a dose contact your doctor or nurse.

You must always use the correct dose of NEUPOGEN®. Too little NEUPOGEN® may not protect you against infections, and too much NEUPOGEN® may cause too many neutrophils to be in your blood. Your doctor will determine your/your child’s correct dose based on your/your child's body weight.

If you are giving someone else NEUPOGEN® injections, it is important that you know how to inject NEUPOGEN®, how much to inject, and how often to inject NEUPOGEN®.

NEUPOGEN® is available as a liquid in vials or in prefilled syringes. When you receive your NEUPOGEN®, always check to see that:

- The name NEUPOGEN® appears on the package and vial or prefilled syringe label.

- The expiration date on the vial or prefilled syringe label has not passed. You should not use a vial or prefilled syringe after the date on the label.

- The strength of the NEUPOGEN® (number of micrograms in the colored dot on the package containing the vial or prefilled syringe) is the same as your doctor prescribed.

- The NEUPOGEN® liquid in the vial or in the prefilled syringe is clear and colorless. Do not use NEUPOGEN® if the contents of the vial or prefilled syringe appear discolored or cloudy, or if the vial or prefilled syringe appears to contain lumps, flakes, or particles.

only use the syringe that your doctor prescribes.

Your doctor or nurse will give you instructions on how to measure the correct dose of NEUPOGEN®. This dose will be measured in milliliters. You should only use a syringe that is marked in tenths of milliliters, or mL (for example, 0.2 mL). The doctor or nurse may refer to an mL as a cc (1 mL = 1 cc). If you do not use the correct syringe, you or your child could receive too much or too little NEUPOGEN®.

Only use disposable syringes and needles. Use the syringes only once and dispose of them as instructed by your doctor or nurse.

IMPORTANT: TO HELP AVOID POSSIBLE INFECTION, YOU SHOULD FOLLOW THESE INSTRUCTIONS.

Setting up for an injection

1. Find a clean flat working surface, such as a table.
2. Remove the vial or prefilled syringe of NEUPOGEN® from the refrigerator. Allow NEUPOGEN® to reach room temperature (this takes about 30 minutes). Vials or prefilled syringes should be used only once. DO NOT SHAKE THE VIAL OR PREFILLED SYRINGE. Shaking may damage the NEUPOGEN®. If the vial or prefilled syringe has been shaken vigorously, the solution may appear foamy and it should not be used.
3. Assemble the supplies you will need for an injection:
  - NEUPOGEN® vial and disposable syringe and needle
  - NEUPOGEN® prefilled syringe with transparent (clear) plastic orange needle guard attached
  - two alcohol swabs and one cotton ball or gauze pad
  - puncture-proof disposal container
  4. Wash your hands with soap and warm water.

HOW TO PREPARE THE DOSE OF NEUPOGEN® IN VIALS OR PREFILLED SYRINGES

If you are using NEUPOGEN® in a vial, follow the instructions in Section A. If you are using NEUPOGEN® in a prefilled syringe, go to Section B.

Section A. Preparing the dose of NEUPOGEN® in a vial

1. Take the cap off the vial. Clean the rubber stopper with one alcohol swab.

2. Check the package containing the syringe. If the package has been opened or damaged, do not use that syringe. Dispose of that syringe in the puncture-proof disposal container. If the syringe package is undamaged, open the package and remove the syringe.

3. Pull the needle cover straight off the syringe. Then, pull back the plunger and draw air into the syringe. The amount of air drawn into the syringe should be the same amount (mL or cc) as the dose of NEUPOGEN® that your doctor prescribed.

4. Keep the vial on your flat working surface and insert the needle straight down through the rubber stopper. Do not put the needle through the rubber stopper more than once.

5. Push the plunger of the syringe down and inject the air from the syringe into the vial of NEUPOGEN®.

6. Keeping the needle in the vial, turn the vial upside down. Make sure that the NEUPOGEN® liquid is covering the tip of the needle.

7. Keeping the vial upside down, slowly pull back on the plunger to fill the syringe with NEUPOGEN® liquid to the number (mL or cc) that matches the dose your doctor prescribed.

8. Keeping the needle in the vial, check for air bubbles in the syringe. If there are air bubbles, gently tap the syringe with your fingers until the air bubbles rise to the top of the syringe. Then slowly push the plunger up to force the air bubbles out of the syringe.

9. Keeping the tip of the needle in the liquid, once again pull the plunger back to the number on the syringe that matches your dose. Check again for air bubbles. The air in the syringe will not hurt you, but too large an air bubble can reduce your dose of NEUPOGEN®. If there are still air bubbles, repeat the steps above to remove them.

10. Check again to make sure that you have the correct dose in the syringe. It is important that you use the exact dose prescribed by your doctor. Remove the syringe from the vial but do not lay it down or let the needle touch anything. (Go to “Injecting the dose of NEUPOGEN®”).

Section B. Preparing the dose of NEUPOGEN® in a prefilled syringe

1. Remove the syringe from the package and the tray. Check to see that the plastic orange needle guard is covering the barrel of the glass syringe. DO NOT push the orange needle guard over the needle cover before injection. This may activate or lock the needle guard. If the orange needle guard is covering the needle that means it has been activated. Do NOT use that syringe. Dispose of that syringe in the puncture-proof disposal container. Use a new syringe from the package.
2. Hold the syringe barrel through the needle guard windows with the needle pointing up. Holding the syringe with the needle pointing up helps to prevent medicine from leaking out of the needle. Carefully pull the needle cover straight off.
3. Check the syringe for air bubbles. If there are air bubbles, gently tap the syringe with your fingers until the air bubbles rise to the top of the syringe. Slowly push the plunger up to force the air bubbles out of the syringe.
4. Push the plunger up to the number (mL) on the syringe that matches the dose of NEUPOGEN® that your doctor prescribed.
5. Check again to make sure the correct dose of NEUPOGEN® is in the syringe.
6. Gently place the prefilled syringe with the window flat on your clean working surface so that the needle does not touch anything.

Selecting and preparing the injection site

1. Choose an injection site. Four recommended injection sites for NEUPOGEN® are:
  - The outer area of your upper arms
  - The abdomen, except for the two inch area around your navel
  - The front of your middle thighs
  - The upper outer areas of your buttocks
  Choose a new site each time you inject NEUPOGEN®. Choosing a new site can help avoid soreness at any one site. Do not inject NEUPOGEN® into an area that is tender, red, bruised, or hard or that has scars or stretch marks.
2. Clean the injection site with a new alcohol swab.

Injecting the dose of NEUPOGEN®

1. For injecting the dose of NEUPOGEN® from a vial, remove the syringe and needle from the vial. For injecting the dose of NEUPOGEN® from a prefilled syringe, pick up the prefilled syringe from your clean flat working surface by grabbing the sides of the needle guard with your thumb and forefinger.
2. Hold the syringe in the hand you will use to inject NEUPOGEN®. Use the other hand to pinch a fold of skin at the cleaned injection site. Note: If using a prefilled syringe with a needle guard, hold the syringe barrel through the needle guard windows when giving the injection.
3. Holding the syringe like a pencil, use a quick “dart-like” motion to insert the needle either straight up and down (90 degree angle) or at a slight angle (45 degrees) into the skin.
4. After the needle is inserted, let go of the skin. Pull the plunger back slightly. If no blood appears, slowly push down on the plunger all the way, until all the NEUPOGEN® is injected. If blood comes into the syringe, do not inject NEUPOGEN®, because the needle has entered a blood vessel. Withdraw the syringe and discard it in the puncture-proof container. Repeat the steps to prepare a new syringe (or get a new prefilled syringe) and choose and clean a new injection site. Remember to check again for blood before injecting NEUPOGEN®.
5. When the syringe is empty, pull the needle out of the skin and place a cotton ball or gauze over the injection site and press for several seconds.
6. Use a prefilled syringe with the needle guard or a syringe and vial only once. If you are using a syringe, DO NOT put the needle cover (the cap) back on the needle. Discard the vial with any remaining NEUPOGEN® liquid.

Activating the Needle Guard for the prefilled syringe after the injection has been given

1. After injecting NEUPOGEN® from the prefilled syringe, do not recap the needle. Keep your hands behind the needle at all times. While holding the clear plastic finger grip of the syringe with one hand, grasp the orange needle guard with your free hand and slide the orange needle guard over the needle until the needle is completely covered and the needle guard clicks into place. NOTE: If an audible click is not heard, the needle guard may not be completely activated.
2. Place the prefilled syringe with the activated needle guard into a puncture-proof container for proper disposal as described below.

Disposal of syringes, needles, vials and needle guards

You should always follow the instructions given by your doctor, nurse, or pharmacist on how to properly dispose of containers with used syringes, needles, vials and needle guards. There may be special state and local laws for disposal of used needles and syringes.

- Place all used needles, needle covers, syringes, and vials (empty or unused contents) into a “Sharps” container given to you by your doctor or pharmacist or in a hard-plastic container with a screw-on cap, or a metal container with a plastic lid, such as a coffee can, labeled “used syringes.” If a metal container is used, cut a small hole in the plastic lid and tape the lid to the metal container. If a hard-plastic container is used, always screw the cap on tightly after each use.
- Do not use glass or clear plastic containers.
- When the container is full, tape around the cap or lid to make sure the cap or lid does not come off. Do not throw the container in the household trash. Do not recycle.
- Always keep the container out of the reach of children.

How should NEUPOGEN® be stored?

NEUPOGEN® should be stored in the refrigerator at 2º to 8ºC (36º to 46ºF), but not in the freezer. Avoid shaking NEUPOGEN®. If NEUPOGEN® is accidentally frozen, allow it to thaw in the refrigerator before giving the next dose. However, if it is frozen a second time, do not use it and contact your doctor or nurse for further instructions. NEUPOGEN® can be left out at room temperature for up to 24 hours. Do not leave NEUPOGEN® in direct sunlight. If you have any questions about storage or how to carry NEUPOGEN® when you travel, contact your doctor, nurse, or pharmacist.

What are the ingredients in NEUPOGEN®?

Each syringe and vial contains Filgrastim in a sterile, clear, colorless, preservative-free solution containing acetate, sorbitol, polysorbate 80, and sodium.

The needle cover on the single-use prefilled syringe contains dry natural rubber (latex), which should not be handled by persons sensitive to this substance.

[Amgen Logo]

Manufactured by:
Amgen Manufacturing, Limited,
a subsidiary of Amgen Inc.
One Amgen Center Drive
Thousand Oaks, California 91320-1799 U.S.A.

3xxxxxx

© 1991-2007 Amgen Inc. All rights reserved.

v8.1 - Issue Date: 09/2007

PRINCIPAL DISPLAY PANEL

NEUPOGEN®: